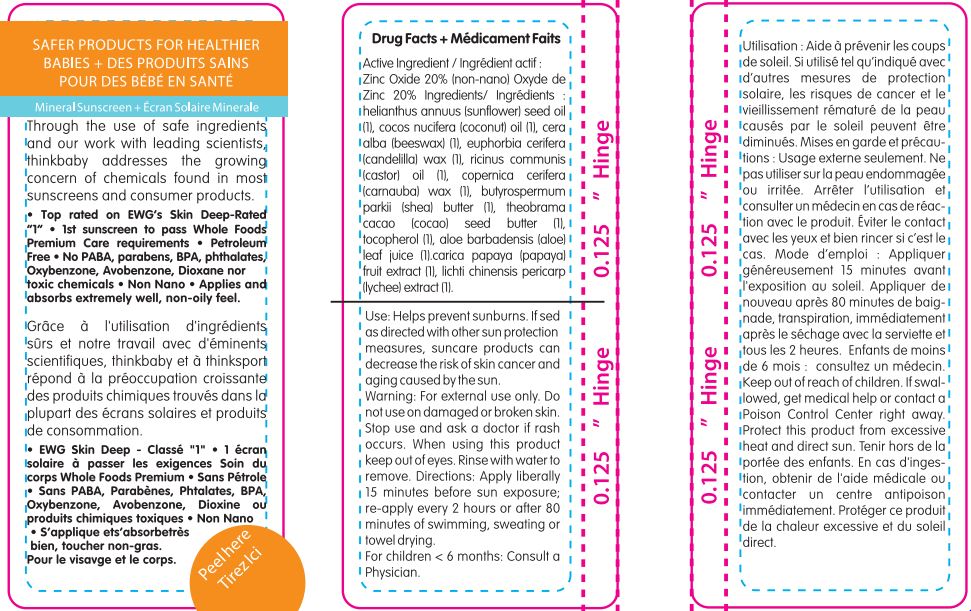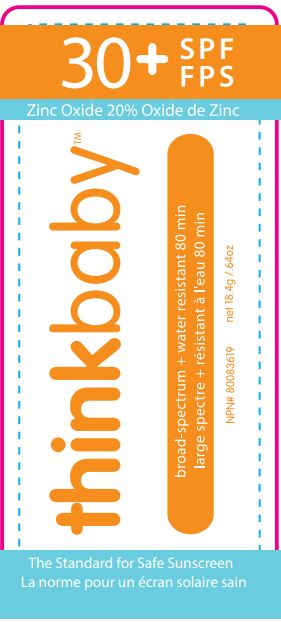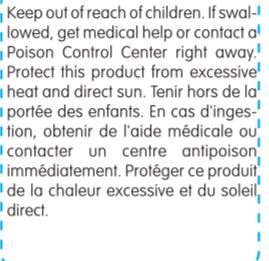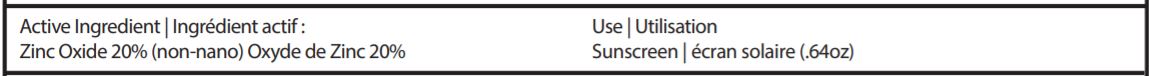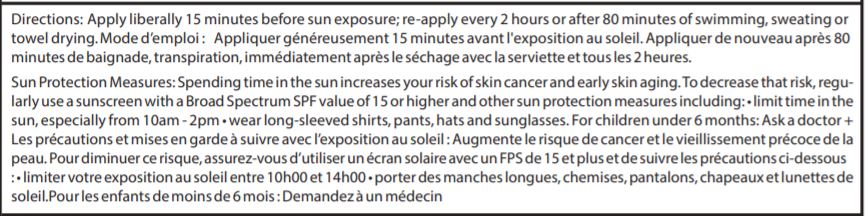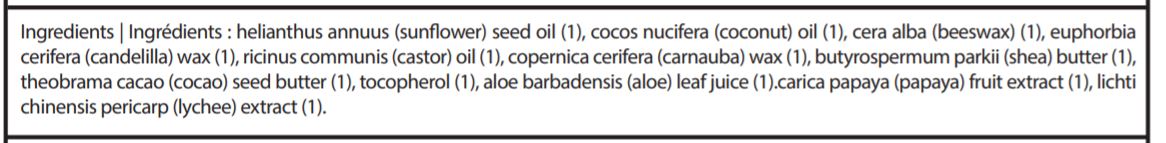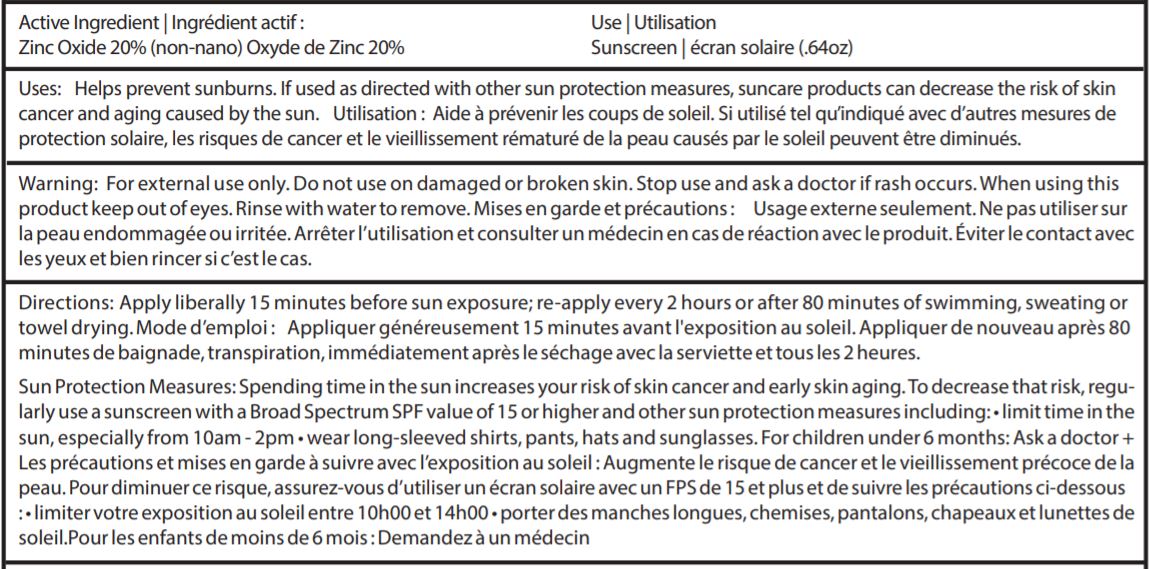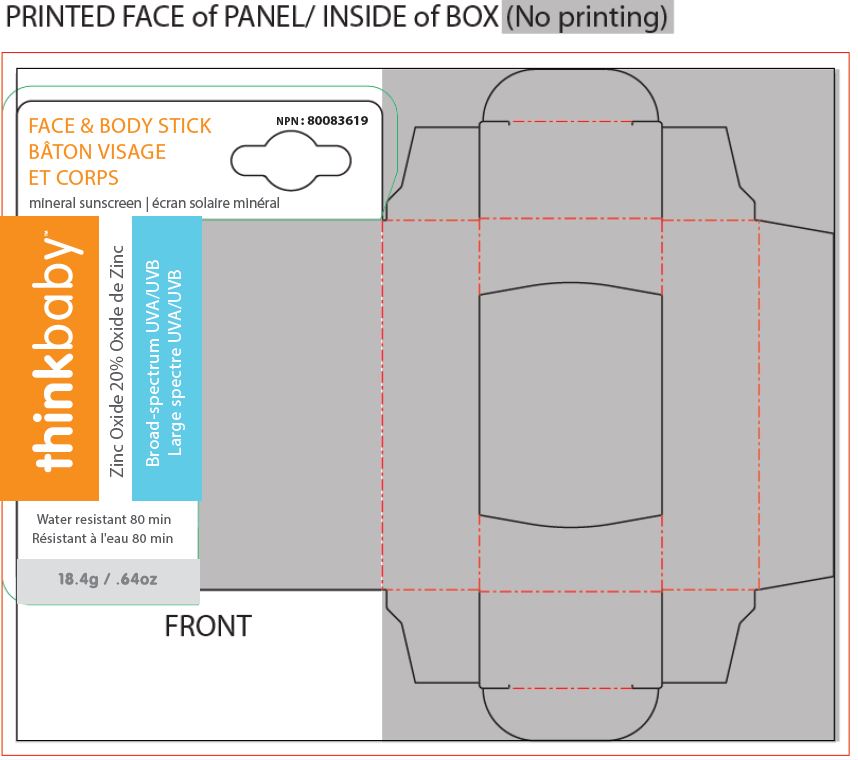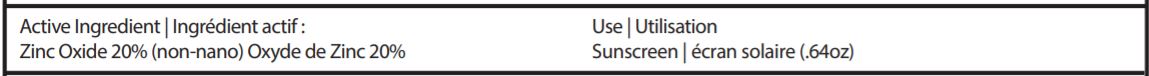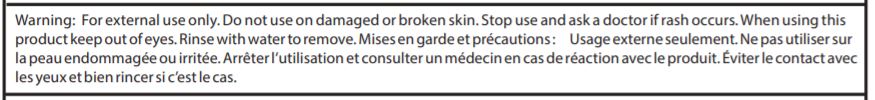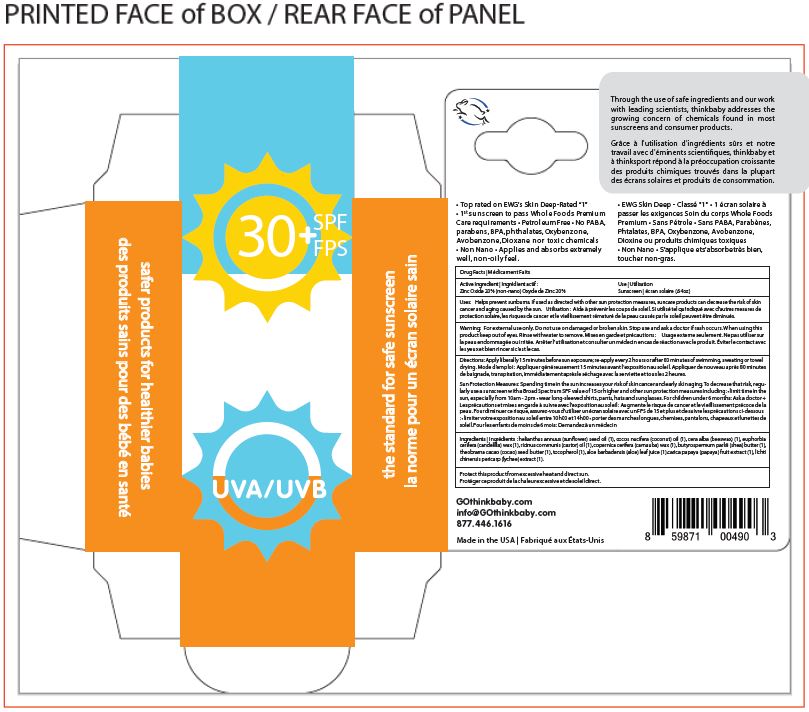 DRUG LABEL: Sunscreen
NDC: 62932-212 | Form: STICK
Manufacturer: Private Label Select Ltd CO
Category: otc | Type: HUMAN OTC DRUG LABEL
Date: 20191231

ACTIVE INGREDIENTS: ZINC OXIDE 20 g/100 g
INACTIVE INGREDIENTS: COCONUT OIL; SUNFLOWER OIL; .BETA.-TOCOPHEROL; CANDELILLA WAX; SHEA BUTTER; CASTOR OIL; WHITE WAX; CARNAUBA WAX; COCOA BUTTER; ALOE VERA LEAF

Think Operations, Think Baby SPF 30 Stick Canadian